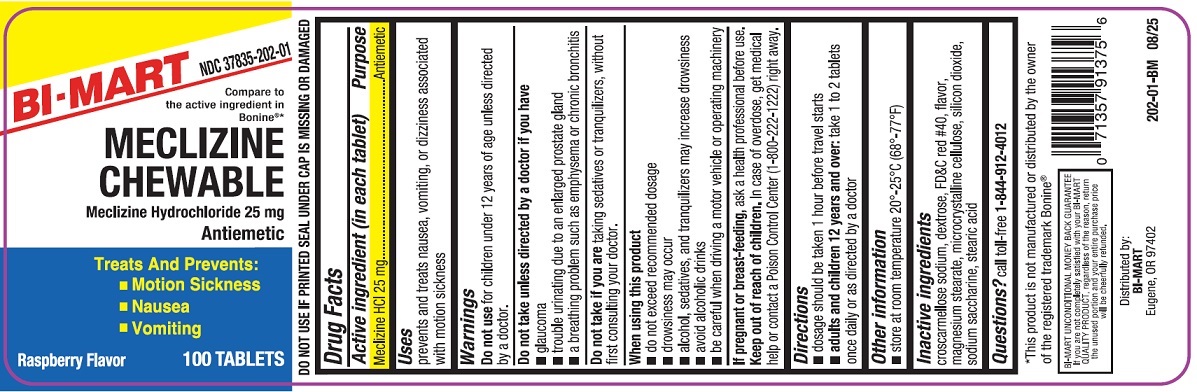 DRUG LABEL: MECLIZINE
NDC: 37835-202 | Form: TABLET, CHEWABLE
Manufacturer: Bi-Mart
Category: otc | Type: HUMAN OTC DRUG LABEL
Date: 20260113

ACTIVE INGREDIENTS: MECLIZINE HYDROCHLORIDE 25 mg/1 1
INACTIVE INGREDIENTS: CROSCARMELLOSE SODIUM; DEXTROSE; FD&C RED NO. 40; MAGNESIUM STEARATE; CELLULOSE, MICROCRYSTALLINE; SILICON DIOXIDE; SACCHARIN SODIUM; STEARIC ACID; RASPBERRY

Drug Facts

Active ingredient (in each tablet)

Meclizine HCl 25mg

Purpose

Antiemetic

Uses

prevents and treats nausea, vomiting or dizziness associated with motion sickness

Warnings

Do not use for children under 12 years of age unless directed by a doctor.

Do not take unless directed by a doctor, if you have

- glaucoma
- trouble urinating due to an enlarged prostate gland
- a breathing problem such as emphysema or chronic bronchitis

Do not take if you aretaking sedatives or tranquilizers, without first consulting your doctor.

When using this product

- do not exceed recommended dosage
- drowsiness may occur
- alcohol, sedatives, and tranquilizers may increase drowsiness
- avoid alcoholic drinks
- use caution when driving a motor vehicle or operating machinery

If pregnant or breast-feeding,

ask a health professional before use.

Keep out of reach of children.

In case of overdose, get medical help or contact a Poison Control Center (800-222-1222) right away.

Directions

- doage should be taken 1 hour before travel starts
- adults and children 12 years and over: take 1 to 2 tablets once daily or as directed by doctor

Other information

- store at room temperature 20°-25°C (68°-77°F)
- DO NOT USE IF PRINTED SEAL UNDER CAP IS MISSING OR DAMAGED

Inactive ingredients

Croscarmellose sodium, dextrose, FD&C Red#40, raspberry flavor, magnesium stearate, microcrystalline cellulose, silicon dioxide, sodium saccharine, stearic acid

Questions or comments?

call toll free 1-844-912-4012